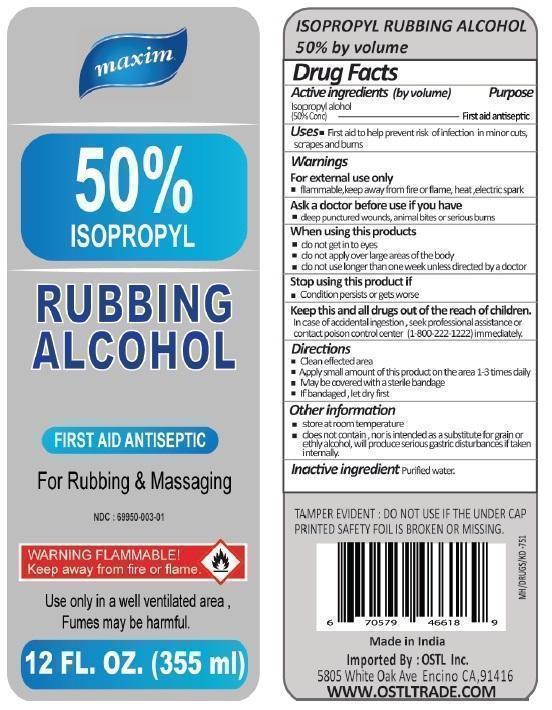 DRUG LABEL: maxim 50% ISOPROPYL RUBBING ALCOHOL
NDC: 69950-003 | Form: LIQUID
Manufacturer: OSTL, INC.
Category: otc | Type: HUMAN OTC DRUG LABEL
Date: 20191220

ACTIVE INGREDIENTS: ISOPROPYL ALCOHOL 50 mL/100 mL
INACTIVE INGREDIENTS: WATER

maxim 50% ISOPROPYL RUBBING ALCOHOL

Active ingredients (by volume)

Isopropyl alcohol (50% Conc)

Purpose

First aid antiseptic

Keep this and all drugs out of the reach of children.

In case of accidental ingestion, seek professional assistance or contact poison control center (1-800-222-1222) immediately.

INDICATIONS AND USAGE

Uses • First aid to help prevent risk of infection in minor cuts, scrapes and burns

Warnings

For external use only

• flammable, keep away from fire or flame, heat, electric spark

Ask a doctor before use if you have

• deep punctured wounds, animals bites or serious burns

When using this products

• do not get into eyes

• do not apply over large areas of the body

• do not use longer than one week unless directed by a doctor

Stop using this product if

• Condition persists or gets worse

Directions

• Clean affected area

• Apply small amount of this product on the area 1-3 times daily

• May be covered with a sterile bandage

• If bandaged, let dry first

Inactive ingredient Purified water

Other information

• store at room temperature

• does not contain, nor is intended as a substitute for grain or ethyl alcohol, will produce serious gastric disturbances if taken internally.

Use only in a well ventilated area, Fumes may be harmful.

TAMPER EVIDENT : DO NOT USE IF THE UNDER CAP PRINTED SAFETY FOIL IS BROKEN OR MISSING.

Made in India

Imported By : OSTL Inc.

5805 White Oak Ave Encino CA, 91416

WWW.OSTLTRADE.COM